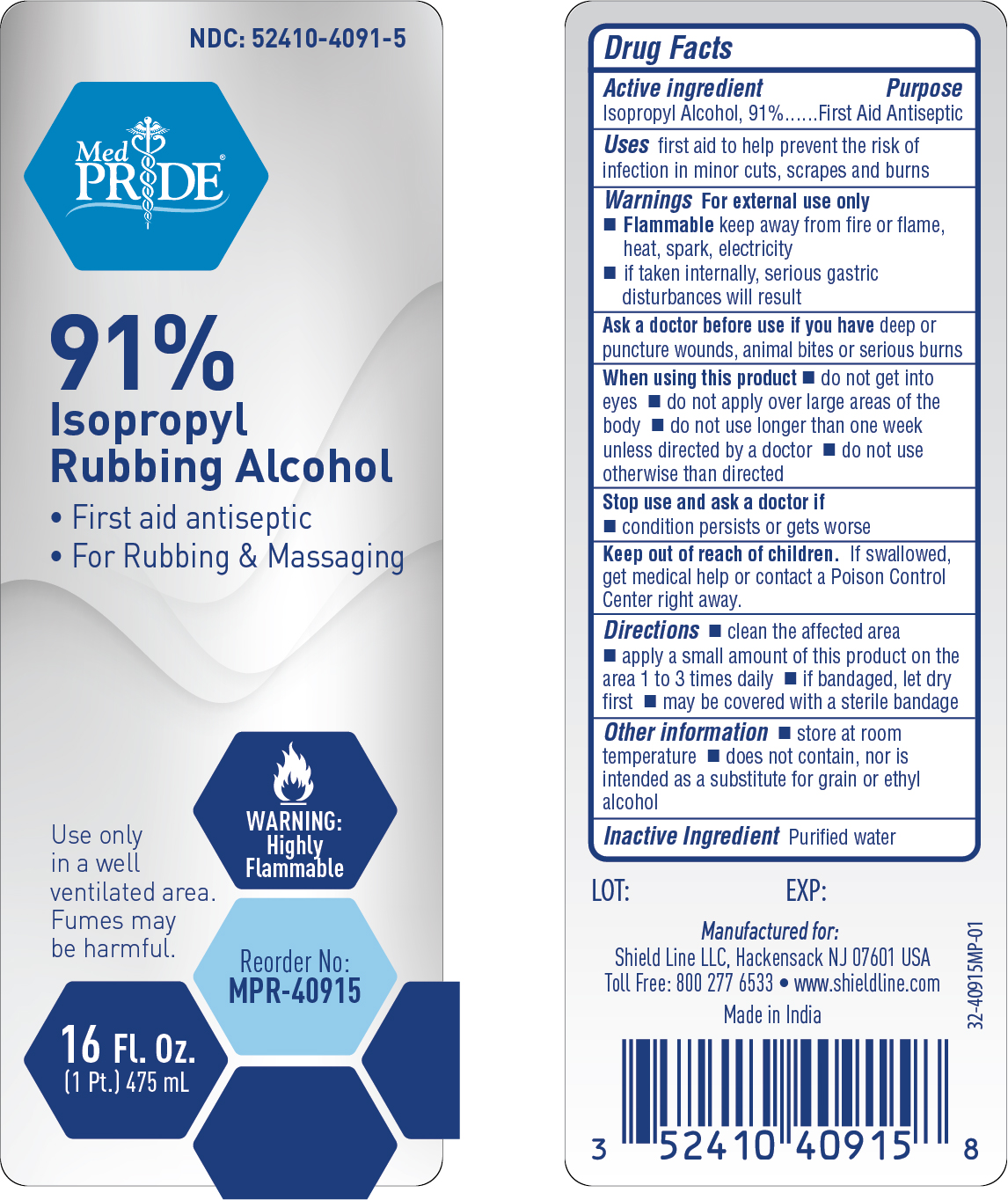 DRUG LABEL: MedPride 91% Rubbing Alcohol
NDC: 52410-4091 | Form: LIQUID
Manufacturer: Shield Line LLC
Category: otc | Type: HUMAN OTC DRUG LABEL
Date: 20240417

ACTIVE INGREDIENTS: ISOPROPYL ALCOHOL 91 mL/100 mL
INACTIVE INGREDIENTS: WATER

MedPride 91 % Isopropyl Alcohol

Active ingredient

Isopropyl Alcohol 91%

Purpose

First Aid Antiseptic

Uses

first aid to help prevent risk of infection in minor cuts, scrapes and burns

Warnings

For external use only

■ Flammable, keep away from fire and flame, heat spark or electricity

■ if taken internally, serious gastric disturbances will result

Ask a doctor before use if you have

■ deep or puncture wounds, animal bites or serious burns

When using this product

■ do not get into your eyes ■ do not apply over large areas of the body ■ do not use longer than one week unless directed by a doctor

■ do not use otherwise than directed

Stop use and ask a doctor if

■ condition persists or gets worse

Keep out of reach of children

If swallowed, get medical help or contact a Poison Control Center right away.

Directions

■ clean affected area ■ apply a small amount of this product on the area 1 to 3 times daily

■ if bandaged, let dry first ■ may be covered with a sterile bandage

Other information

■ store at room temperature

■ does not contain nor is intended as a substitute for grain or ethyl alcohol

Inactive Ingredient

purified water